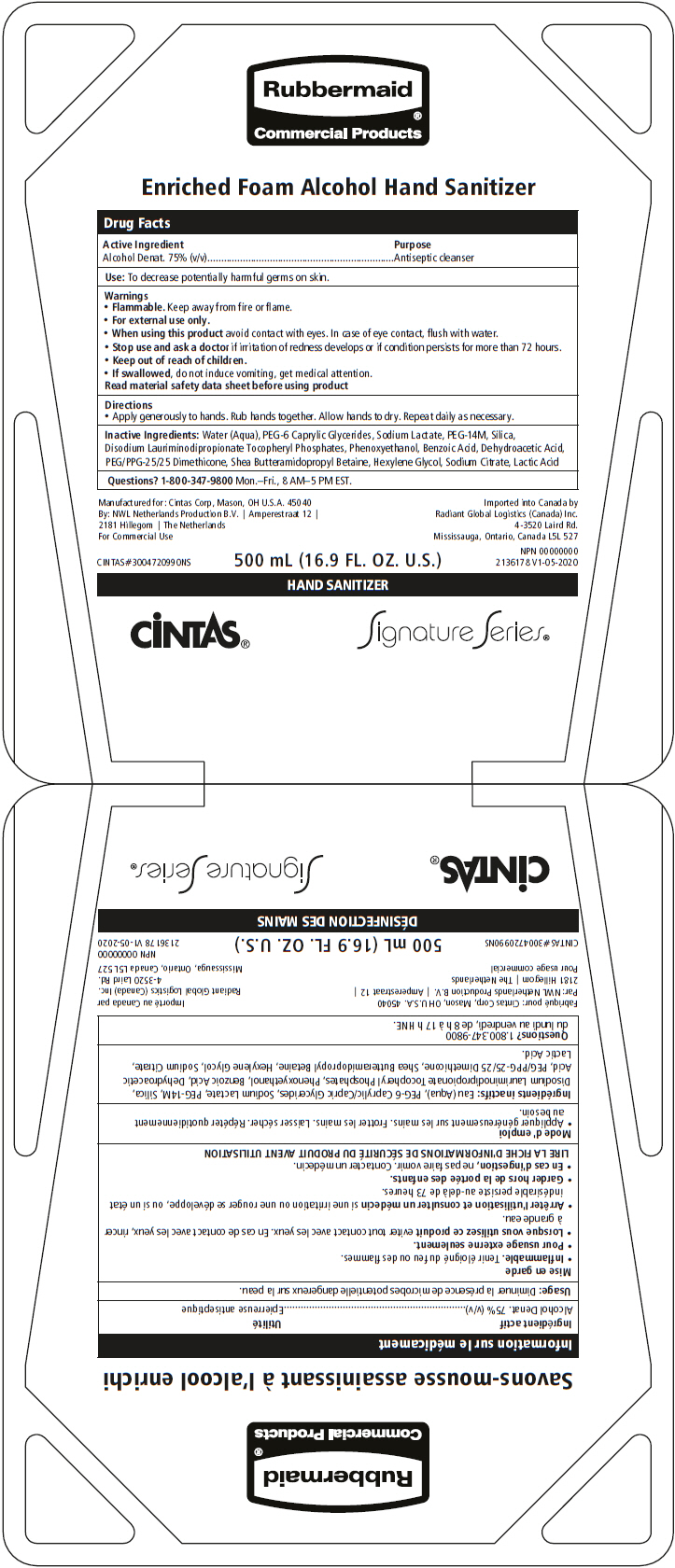 DRUG LABEL: Signature Series Enriched Foam Alcohol Hand Sanitizer
NDC: 42961-017 | Form: LIQUID
Manufacturer: Cintas Corporation
Category: otc | Type: HUMAN OTC DRUG LABEL
Date: 20241115

ACTIVE INGREDIENTS: ALCOHOL 75 mL/100 mL
INACTIVE INGREDIENTS: WATER; CAPRYLOCAPROYL POLYOXYLGLYCERIDES 6; SODIUM LACTATE; POLYETHYLENE OXIDE 600000; SILICON DIOXIDE; DISODIUM LAURIMINODIPROPIONATE TOCOPHERYL PHOSPHATES; PHENOXYETHANOL; BENZOIC ACID; DEHYDROACETIC ACID; PEG/PPG-25/25 DIMETHICONE; HEXYLENE GLYCOL; SODIUM CITRATE, UNSPECIFIED FORM; LACTIC ACID, UNSPECIFIED FORM

Signature Series® Enriched Foam Alcohol Hand Sanitizer

Drug Facts

Active Ingredient

Alcohol Denat. 75% (v/v)

Purpose

Antiseptic cleanser

Use

To decrease potentially harmful germs on skin.

Warnings

- Flammable. Keep away from fire or flame.
- For external use only.

- When using this product avoid contact with eyes. In case of eye contact, flush with water.

- Stop use and ask a doctor if irritation of redness develops or if condition persists for more than 72 hours.

- Keep out of reach of children.
- If swallowed, do not induce vomiting, get medical attention.

Read material safety data sheet before using product

Directions

- Apply generously to hands. Rub hands together. Allow hands to dry. Repeat daily as necessary.

Inactive Ingredients

Water (Aqua), PEG-6 Caprylic Glycerides, Sodium Lactate, PEG-14M, Silica, Disodium Lauriminodipropionate Tocopheryl Phosphates, Phenoxyethanol, Benzoic Acid, Dehydroacetic Acid, PEG/PPG-25/25 Dimethicone, Shea Butteramidopropyl Betaine, Hexylene Glycol, Sodium Citrate, Lactic Acid

Questions?

1-800-347-9800 Mon.–Fri., 8 AM–5 PM EST.

PRINCIPAL DISPLAY PANEL - 500 mL Pouch Box

Rubbermaid®
Commercial Products

Enriched Foam Alcohol Hand Sanitizer

500 mL (16.9 FL. OZ. U.S.)

HAND SANITIZER

CiNTAS®
Signature Series®